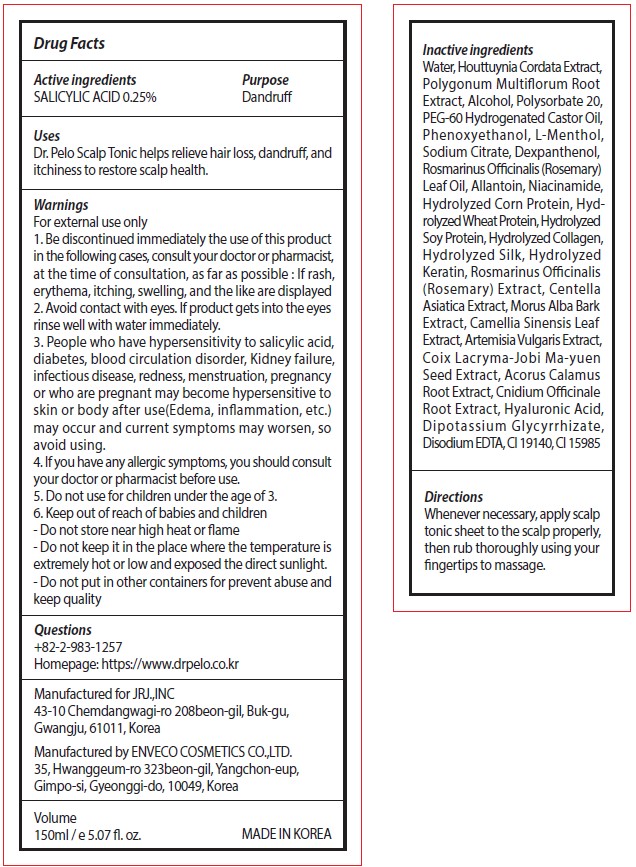 DRUG LABEL: Dr. Pelo Scalp Tonic
NDC: 81702-203 | Form: LIQUID
Manufacturer: JRJ.,INC
Category: otc | Type: HUMAN OTC DRUG LABEL
Date: 20210323

ACTIVE INGREDIENTS: SALICYLIC ACID 0.25 mg/100 mL
INACTIVE INGREDIENTS: ROSEMARY; CENTELLA ASIATICA WHOLE; EDETATE DISODIUM ANHYDROUS; FD&C YELLOW NO. 6; WATER; HOUTTUYNIA CORDATA FLOWERING TOP; ALCOHOL; SODIUM CITRATE, UNSPECIFIED FORM; DEXPANTHENOL; ARTEMISIA VULGARIS ROOT; ACORUS CALAMUS ROOT; HYALURONIC ACID; FD&C YELLOW NO. 5; ALLANTOIN; HYDROLYZED WHEAT PROTEIN (ENZYMATIC, 3000 MW); HYDROLYZED SOY PROTEIN (ENZYMATIC; 2000 MW); REYNOUTRIA MULTIFLORA ROOT; PHENOXYETHANOL; LEVOMENTHOL; ROSEMARY OIL; COIX LACRYMA-JOBI VAR. MA-YUEN SEED; CNIDIUM OFFICINALE ROOT; GLYCYRRHIZINATE DIPOTASSIUM; POLYSORBATE 20; PEG-60 HYDROGENATED CASTOR OIL; NIACINAMIDE; MORUS ALBA BARK; GREEN TEA LEAF

81702-203 Dr. Pelo Scalp Tonic

Active ingredients

SALICYLIC ACID 0.25%

Purpose

Dandruff

Uses

Dr. Pelo Scalp Tonic helps relieve hair loss, dandruff, and itchiness to restore scalp health.

Warnings

For external use only

Stop use

1. Be discontinued immediately the use of this product in the following cases, consult your doctor or pharmacist, at the time of consultation, as far as possible : If rash, erythema, itching, swelling, and the like are displayed

2. Avoid contact with eyes. If product gets into the eyes rinse well with water immediately.

3. People who have hypersensitivity to salicylic acid, diabetes, blood circulation disorder, Kidney failure, infectious disease, redness, menstruation, pregnancy or who are pregnant may become hypersensitive to skin or body after use(Edema, inflammation, etc.) may occur and current symptoms may worsen, so avoid using.
4. If you have any allergic symptoms, you should consult your doctor or pharmacist before use.

Do not use

5. Do not use for children under the age of 3.

Keep out of reach of children

6. Keep out of reach of babies and children

Directions

Whenever necessary, apply scalp tonic sheet to the scalp properly, then rub thoroughly using your fingertips to massage.

Inactive ingredients

Water, Houttuynia Cordata Extract, Polygonum Multiflorum Root Extract, Alcohol, Polysorbate 20, PEG-60 Hydrogenated Castor Oil, Phenoxyethanol, L-Menthol, Sodium Citrate, Dexpanthenol, Rosmarinus Officinalis (Rosemary) Leaf Oil, Allantoin, Niacinamide,
Hydrolyzed Corn Protein, Hydrolyzed Wheat Protein, Hydrolyzed Soy Protein, Hydrolyzed Collagen, Hydrolyzed Silk, Hydrolyzed
Keratin, Rosmarinus Officinalis (Rosemary) Extract, Centella Asiatica Extract, Morus Alba Bark Extract, Camellia Sinensis Leaf
Extract, Artemisia Vulgaris Extract, Coix Lacryma-Jobi Ma-yuen Seed Extract, Acorus Calamus Root Extract, Cnidium Officinale Root Extract, Hyaluronic Acid, Dipotassium Glycyrrhizate, Disodium EDTA, CI 19140, CI 15985

Other information

- Do not store near high heat or flame
- Do not keep it in the place where the temperature is extremely hot or low and exposed the direct sunlight.
- Do not put in other containers for prevent abuse and keep quality